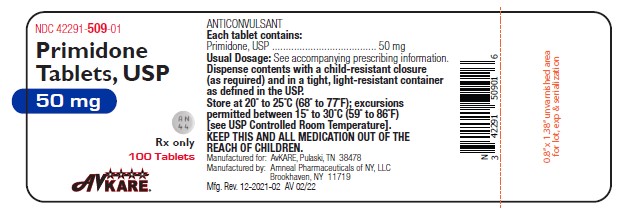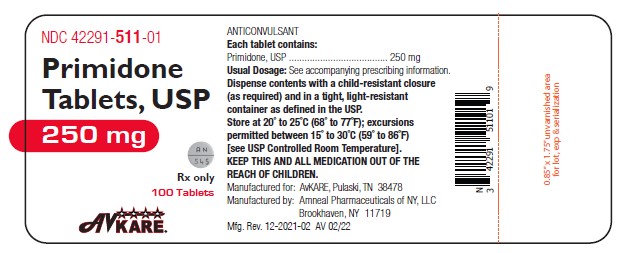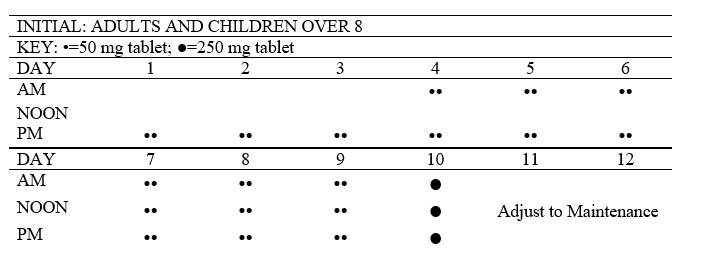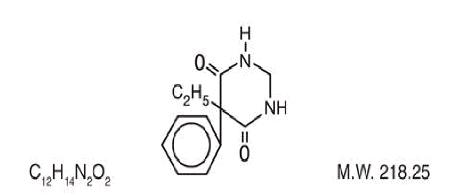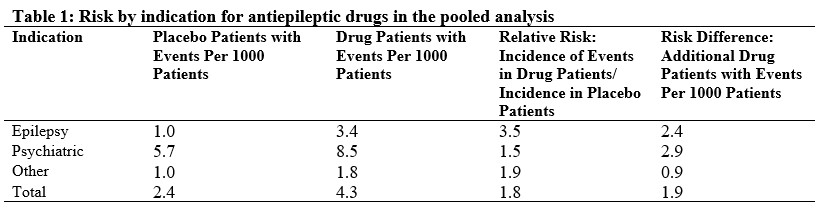 DRUG LABEL: Primidone
NDC: 42291-509 | Form: TABLET
Manufacturer: AvKARE
Category: prescription | Type: HUMAN PRESCRIPTION DRUG LABEL
Date: 20260114

ACTIVE INGREDIENTS: PRIMIDONE 50 mg/1 1
INACTIVE INGREDIENTS: STARCH, CORN; LACTOSE MONOHYDRATE; MAGNESIUM STEARATE; CELLULOSE, MICROCRYSTALLINE; SODIUM LAURYL SULFATE; SODIUM STARCH GLYCOLATE TYPE A POTATO; METHYLCELLULOSE (100 CPS)

Primidone Tablets, USP
50mg and 250mg

Rx Only

Anticonvulsant

DESCRIPTION

Primidone, USP is a white, crystalline, highly stable substance, M.P. 279-284° C. It is poorly soluble in water (60 mg per 100 mL at 37° C) and in most organic solvents. It possesses no acidic properties, in contrast to its barbiturate analog.

Chemical name: 5-ethyldihydro-5-phenyl-4,6 (1H, 5H)-pyrimidinedione.

Structural formula:

Primidone tablets USP, 50 mg and 250 mg contain the following inactive ingredients: corn starch, lactose monohydrate, magnesium stearate, methyl cellulose, microcrystalline cellulose, sodium lauryl sulfate, sodium starch glycolate.

CLINICAL PHARMACOLOGY

Primidone raises electro- or chemoshock seizure thresholds or alters seizure patterns in experimental animals. The mechanisms(s) of primidone’s antiepileptic action is not known.

Primidone per se has anticonvulsant activity as do its two metabolites, phenobarbital and phenylethylmalonamide (PEMA). In addition to its anticonvulsant activity, PEMA potentiates the anticonvulsant activity of phenobarbital in experimental animals.

INDICATIONS AND USAGE

Primidone tablets used alone or concomitantly with other anticonvulsants, are indicated in the control of grand mal, psychomotor, and focal epileptic seizures. It may control grand mal seizures refractory to other anticonvulsant therapy.

CONTRAINDICATIONS

Primidone is contraindicated in:

1) patients with porphyria and

2) patients who are hypersensitive to phenobarbital

(see CLINICAL PHARMACOLOGY).

WARNINGS

The abrupt withdrawal of antiepileptic medication may precipitate status epilepticus. The therapeutic efficacy of a dosage regimen takes several weeks before it can be assessed.

Suicidal Behavior and Ideation

Antiepileptic drugs (AEDs), including primidone, increase the risk of suicidal thoughts or behavior in patients taking these drugs for any indication. Patients treated with any AED for any indication should be monitored for the emergence or worsening of depression, suicidal thoughts or behavior, and/or any unusual changes in mood or behavior.

Pooled analyses of 199 placebo-controlled clinical trials (mono- and adjunctive therapy) of 11 different AEDs showed that patients randomized to one of the AEDs had approximately twice the risk (adjusted Relative Risk 1.8, 95% CI:1.2, 2.7) of suicidal thinking or behavior compared to patients randomized to placebo. In these trials, which had a median treatment duration of 12 weeks, the estimated incidence rate of suicidal behavior or ideation among 27,863 AED-treated patients was 0.43%, compared to 0.24% among 16,029 placebo-treated patients, representing an increase of approximately one case of suicidal thinking or behavior for every 530 patients treated. There were four suicides in drug-treated patients in the trials and none in placebo-treated patients, but the number is too small to allow any conclusion about drug effect on suicide.

The increased risk of suicidal thoughts or behavior with AEDs was observed as early as one week after starting drug treatment with AEDs and persisted for the duration of treatment assessed. Because most trials included in the analysis did not extend beyond 24 weeks, the risk of suicidal thoughts or behavior beyond 24 weeks could not be assessed.

The risk of suicidal thoughts or behavior was generally consistent among drugs in the data analyzed. The finding of increased risk with AEDs of varying mechanisms of action and across a range of indications suggests that the risk applies to all AEDs used for any indication. The risk did not vary substantially by age (5 to 100 years) in the clinical trials analyzed.

Table 1 shows absolute and relative risk by indication for all evaluated AEDs.

The relative risk for suicidal thoughts or behavior was higher in clinical trials for epilepsy than in clinical trials for psychiatric or other conditions, but the absolute risk differences were similar for the epilepsy and psychiatric indications.

Anyone considering prescribing primidone or any other AED must balance the risk of suicidal thoughts or behavior with the risk of untreated illness. Epilepsy and many other illnesses for which AEDs are prescribed are themselves associated with morbidity and mortality and an increased risk of suicidal thoughts and behavior. Should suicidal thoughts and behavior emerge during treatment, the prescriber needs to consider whether the emergence of these symptoms in any given patient may be related to the illness being treated.

Patients, their caregivers, and families should be informed that AEDs increase the risk of suicidal thoughts and behavior and should be advised of the need to be alert for the emergence or worsening of the signs and symptoms of depression, any unusual changes in mood or behavior, or the emergence of suicidal thoughts, behavior, or thoughts about self-harm. Behaviors of concern should be reported immediately to healthcare providers.

Pregnancy

To provide information regarding the effects of in utero exposure to primidone, physicians are advised to recommend that pregnant patients taking primidone enroll in the North American Antiepileptic Drug (NAAED) Pregnancy Registry. This can be done by calling the toll-free number 1-888-233-2334, and must be done by patients themselves. Information on the registry can also be found at the website http://www.aedpregnancyregistry.org/.

The effects of primidone in human pregnancy and nursing infants are unknown.

Recent reports suggest an association between the use of anticonvulsant drugs by women with epilepsy and an elevated incidence of birth defects in children born to these women. Data are more extensive with respect to diphenylhydantoin and phenobarbital, but these are also the most commonly prescribed anticonvulsants; less systematic or anecdotal reports suggest a possible similar association with the use of all known anticonvulsant drugs.

The reports suggesting an elevated incidence of birth defects in children of drug-treated epileptic women cannot be regarded as adequate to prove a definite cause-and-effect relationship.

There are intrinsic methodologic problems in obtaining adequate data on drug teratogenicity in humans, the possibility also exists that other factors leading to birth defects, e.g., genetic factors or the epileptic condition itself, may be more important than drug therapy. The great majority of mothers on anticonvulsant medication deliver normal infants. It is important to note that anticonvulsant drugs should not be discontinued in patients in whom the drug is administered to prevent major seizures because of the strong possibility of precipitating status epilepticus with attendant hypoxia and threat to life. In individual cases where the severity and frequency of the seizure disorders are such that the removal of medication does not pose a serious threat to the patient, discontinuation of the drug may be considered prior to and during pregnancy, although it cannot be said with any confidence that even minor seizures do not pose some hazard to the developing embryo or fetus.

The prescribing physician will wish to weigh these considerations in treating or counseling epileptic women of childbearing potential. Neonatal hemorrhage, with a coagulation defect resembling vitamin K deficiency, has been described in newborns whose mothers were taking primidone and other anticonvulsants. Pregnant women under anticonvulsant therapy should receive prophylactic vitamin K1 therapy for one month prior to, and during, delivery.

PRECAUTIONS

The total daily dosage should not exceed 2g. Since primidone therapy generally extends over prolonged periods, a complete blood count and a sequential multiple analysis-12 (SMA-12) test should be made every six months.

In Nursing Mothers

There is evidence in mothers treated with primidone that the drug appears in breast milk in substantial quantities. Since tests for the presence of primidone in biological fluids are too complex to be carried out in the average clinical laboratory, it is suggested that the presence of undue somnolence and drowsiness in nursing newborns of primidone-treated mothers be taken as an indication that nursing should be discontinued

PATIENT COUNSELING INFORMATION

Suicidal Thoughts and Behavior

Patients, their caregivers, and families should be counseled that AEDs, including primidone, may increase the risk of suicidal thoughts and behavior and should be advised of the need to be alert for the emergence or worsening of symptoms of depression, any unusual changes in mood or behavior, or the emergence of suicidal thoughts, behavior, or thoughts about self-harm. Behaviors of concern should be reported immediately to healthcare providers.

Pregnancy

Patients should be encouraged to enroll in the NAAED Pregnancy Registry if they become pregnant. This registry is collecting information about the safety of antiepileptic drugs during pregnancy. To enroll, patients can call the toll-free number 1-888-233-2334 (see WARNINGS, Pregnancy).

Please refer to the Primidone Medication Guide for more information.

ADVERSE REACTIONS

The most frequently occurring early side effects are ataxia and vertigo. These tend to disappear with continued therapy, or with reduction of initial dosage. Occasionally, the following have been reported: nausea, anorexia, vomiting, fatigue, hyperirritability, emotional disturbances, sexual impotency, diplopia, nystagmus, drowsiness, and morbilliform skin eruptions. Granulocytopenia, agranulocytosis, and red-cell hypoplasia and aplasia, have been reported rarely. These and, occasionally, other persistent or severe side effects may necessitate withdrawal of the drug. Megaloblastic anemia may occur as a rare idiosyncrasy to primidone and to other anticonvulsants. The anemia responds to folic acid without necessity of discontinuing medication.

To report SUSPECTED ADVERSE REACTIONS, contact AvKARE at 1-855-361-3993 or FDA at 1-800-FDA-1088 or www.fda.gov/medwatch.

DOSAGE AND ADMINISTRATION

Dosage

Usual Dosage

Patients 8 years of age and older who have received no previous treatment may be started on primidone tablets according to the following regimen using either 50 mg or scored 250 mg primidone tablets:

Days 1 to 3: 100 to 125 mg at bedtime.
Days 4 to 6: 100 to 125 mg twice a day.
Days 7 to 9: 100 to 125 mg three times a day.
Day 10 to maintenance: 250 mg three times a day.

For most adults and children 8 years of age and over, the usual maintenance dosage is three to four 250 mg primidone tablets in divided doses (250 mg three times a day or four times a day). If required, an increase to five or six 250 mg tablets daily may be made, but daily doses should not exceed 500 mg four times a day.

Dosage should be individualized to provide maximum benefit. In some cases, serum blood level determinations of primidone may be necessary for optimal dosage adjustment. The clinically effective serum level for primidone is between 5 to 12 mcg/mL.

Patients Already Receiving Other Anticonvulsants

Primidone tablets should be started at 100 to 125 mg at bedtime and gradually increased to maintenance level as the other drug is gradually decreased. This regimen should be continued until satisfactory dosage level is achieved for the combination, or the other medication is completely withdrawn. When therapy with primidone tablets alone is the objective, the transition from concomitant therapy should not be completed in less than two weeks.

Pediatric Dosage

For children under 8 years of age, the following regimen may be used:

Days 1 to 3: 50 mg at bedtime.
Days 4 to 6: 50 mg twice a day.
Days 7 to 9: 100 mg twice a day.
Day 10 to maintenance: 125 mg three times a day to 250 mg three times a day.

For children under 8 years of age, the usual maintenance dosage is 125 to 250 mg three times daily or, 10 to 25 mg/kg/day in divided doses.

HOW SUPPLIED

Primidone Tablets, USP, 50 mg are supplied as white, round, flat-faced, bevel-edged tablets, debossed
“AN” above “44” on one side and cut-bisected on the other side.

They are available as follows:

Bottles of 100: NDC 42291-509-01

Bottles of 500: NDC 42291-509-50

Primidone Tablets, USP, 250 mg are supplied as white, round, flat-faced, bevel-edged tablets, debossed
“AN” bisect “545” on one side and plain on the other side.

They are available as follows:

Bottles of 100: NDC 42291-511-01

Bottles of 500: NDC 42291-511-50

STORAGE AND HANDLING

Store at 20°C to 25°C (68°F to 77°F); excursions permitted to 15°C-30°C (59°F- 86°F). [See USP Controlled Room Temperature].

Dispense contents with a child-resistant closure (as required) and in a tight, light-resistant container as defined in the USP.

KEEP THIS AND ALL MEDICATION OUT OF REACH OF CHILDREN.

Manufactured for:

AvKARE

Pulaski, TN 38478

Mfg. Rev. 12-2021-03

AV 01/23

SPL MEDGUIDE SECTION

What is the most important information I should know about primidone?

Like other antiepileptic drugs, primidone may cause suicidal thoughts or actions in a very small number of people, about 1 in 500.

Call a healthcare provider right away if you have any of these symptoms, especially if they are new, worse, or worry you:

thoughts about suicide or dying
attempts to commit suicide
new or worsening depression
new or worsening anxiety
feeling agitated or restless
panic attacks
trouble sleeping (insomnia)
new or worsening irritability
acting aggressive, being angry, or violent
acting on dangerous impulses
an extreme increase in activity and talking (mania)
other unusual changes in behavior or mood

Do not stop taking primidone without first talking to a healthcare provider.

Stopping primidone suddenly can cause serious problems. Stopping a seizure medicine suddenly in a patient who has epilepsy can cause seizures that will not stop (status epilepticus).

Suicidal thoughts or actions can be caused by things other than medicines. If you have suicidal thoughts or actions, your healthcare provider may check for other causes.

How can I watch for early symptoms of suicidal thoughts and actions?

Pay attention to any changes, especially sudden changes, in mood, behaviors, thoughts, or feelings.
Keep all follow-up visits with your healthcare provider as scheduled.

Call your healthcare provider between visits as needed, especially if you are worried about symptoms.

What is primidone?

Primidone is a prescription medicine used alone or with other medicines to treat people with:

generalized tonic-clonic (grand mal) seizures
complex partial (psychomotor) seizures
partial (focal) epileptic seizures

Who should not take primidone?

Do not take primidone if you:

have a genetic disorder called porphyria
are allergic to phenobarbital

What should I tell my healthcare provider before taking primidone?

Before you take primidone, tell your healthcare provider if you:

have or have had depression, mood problems, or suicidal thoughts or behavior
have any other medical conditions
are pregnant or planning to become pregnant. Primidone may harm your unborn baby. Tell your healthcare provider right away if you become pregnant while taking primidone. You and your healthcare provider will decide if you should take primidone while you are pregnant.

If you become pregnant while taking primidone, talk to your healthcare provider about registering with the North American Antiepileptic Drug (NAAED) Pregnancy Registry. You can enroll in this registry by calling 1-888-233-2334. The purpose of this registry is to collect information about the safety of antiepileptic drugs during pregnancy.

are breastfeeding or plan to breastfeed. Primidone can pass into breast milk. Talk to your healthcare provider about the best way to feed your baby if you take primidone.

Tell your healthcare provider about all the medicines you take, including prescription and non-prescription medicines, vitamins, and herbal supplements. Taking primidone with certain other medicines can cause side effects or affect how well they work. Do not start or stop other medicines without talking to your healthcare provider.

Know the medicines you take. Keep a list of them and show it to your healthcare provider and pharmacist each time you get a new medicine.

How should I take primidone tablets?

Take primidone tablets exactly as prescribed. Your healthcare provider will tell you how much primidone tablets to take and when to take it.

Your healthcare provider may change your dose. Do not change your dose without talking to your healthcare provider.
Do not stop taking primidone tablets without first talking to your healthcare provider. Stopping primidone tablets suddenly can cause serious problems.
If you take too much primidone, call your healthcare provider or local Poison Control Center right away.

What should I avoid while taking primidone?

Primidone can make you sleepy or dizzy. Do not drink alcohol or take other drugs that make you sleepy or dizzy while taking primidone without first discussing this with your healthcare provider. Taking primidone with alcohol or drugs that cause sleepiness or dizziness may make your sleepiness or dizziness worse.
Do not drive, operate heavy machinery, or do other dangerous activities until you know how primidone affects you. Primidone can slow your thinking and motor skills.

What are the possible side effects of primidone?

See "What is the most important information I should know about primidone?"

Primidone may cause other serious side effects including:

Sleepiness that can be severe, especially when you first start taking primidone.
Primidone may rarely cause blood problems. Symptoms may include:

fever, swollen glands, or sore throat that come and go or do not go away
frequent infections or an infection that does not go away
tiredness
shortness of breath

Primidone may rarely cause allergic reactions. Symptoms may include:

skin rash
hives
sores in your mouth
blistering or peeling skin

The most common side effects of primidone include:

problems with walking and moving
feelings of dizziness, spinning, or swaying (vertigo)

These are not all the possible side effects of primidone. For more information, ask your healthcare provider or pharmacist.

Tell your healthcare provider if you have any side effect that bothers you or that does not go away.

Call your doctor for medical advice about side effects. You may report side effects to FDA at 1-800-FDA-1088.

How should I store primidone tablets?

Store primidone tablets at room temperature between 68° to 77°F (20° to 25°C) in a tight, light-resistant container.

Keep primidone tablets and all medicines out of the reach of children.

General Information about primidone

Medicines are sometimes prescribed for purposes other than those listed in a Medication Guide. Do not use primidone for a condition for which it was not prescribed. Do not give primidone to other people, even if they have the same symptoms that you have. It may harm them.

This Medication Guide summarizes the most important information about primidone. If you would like more information, talk with your healthcare provider. You can ask your pharmacist or healthcare provider for information about primidone that is written for health professionals.

For more information, call 1-855-361-3993.

What are the ingredients in primidone tablets?

Active Ingredient: primidone

Inactive Ingredients: corn starch, lactose monohydrate, magnesium stearate, methyl cellulose, microcrystalline cellulose, sodium lauryl sulfate, and sodium starch glycolate.

Manufactured for:

AvKARE

Pulaski, TN 38478

Manufactured by:

Amneal Pharmaceuticals of New York, LLC

Brookhaven, NY 11719

This Medication Guide has been approved by the U.S. Food and Drug Administration.

Mfg. Rev. 12-2021-03 AV 02/22